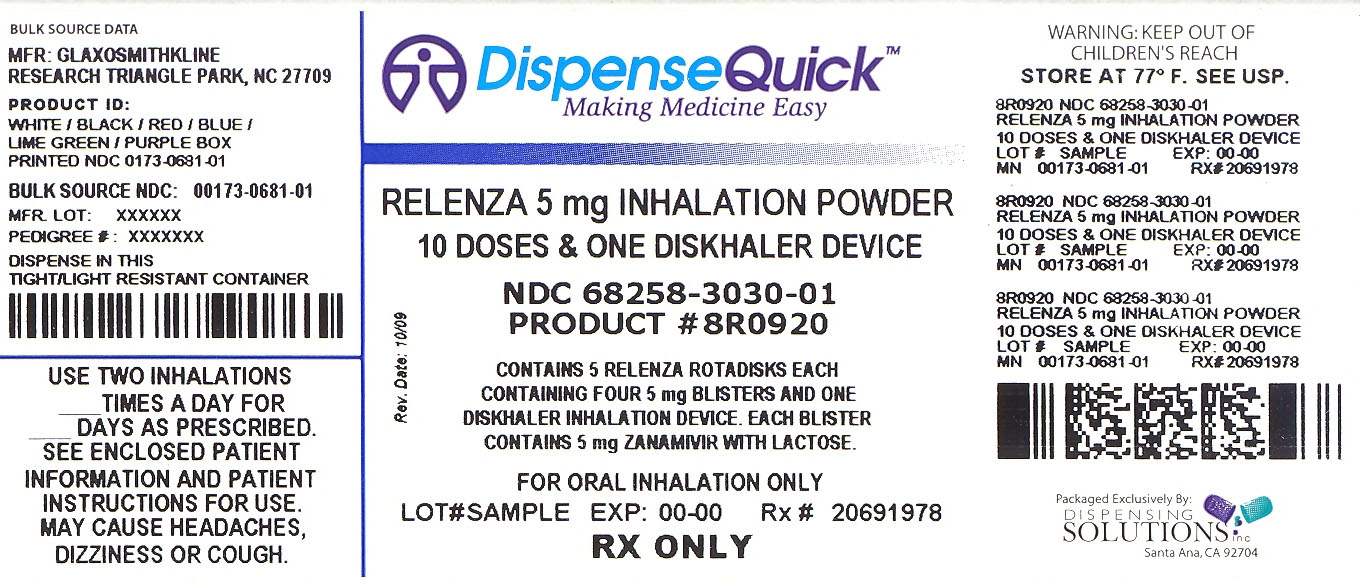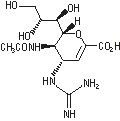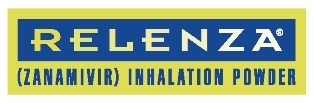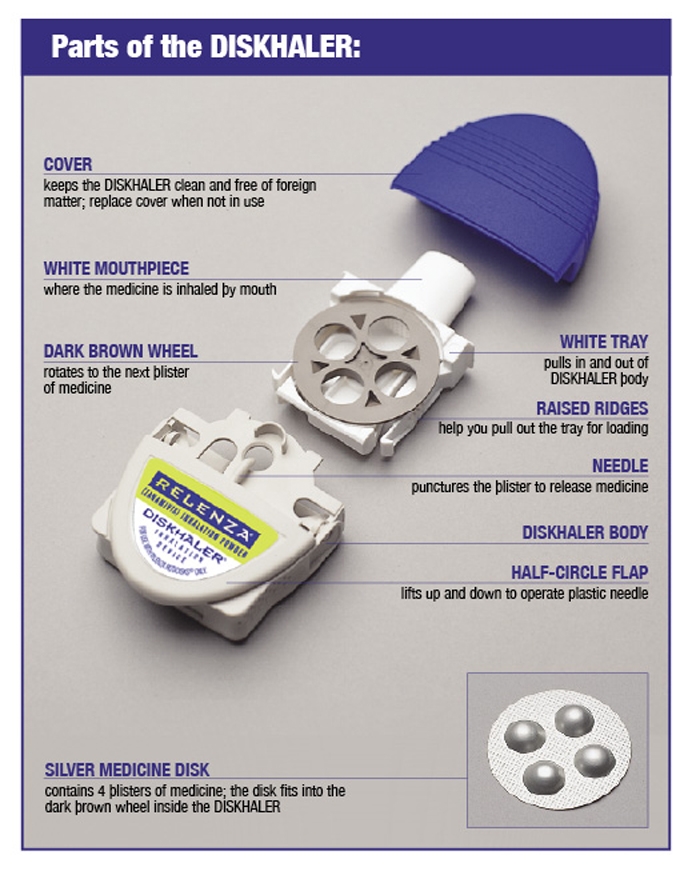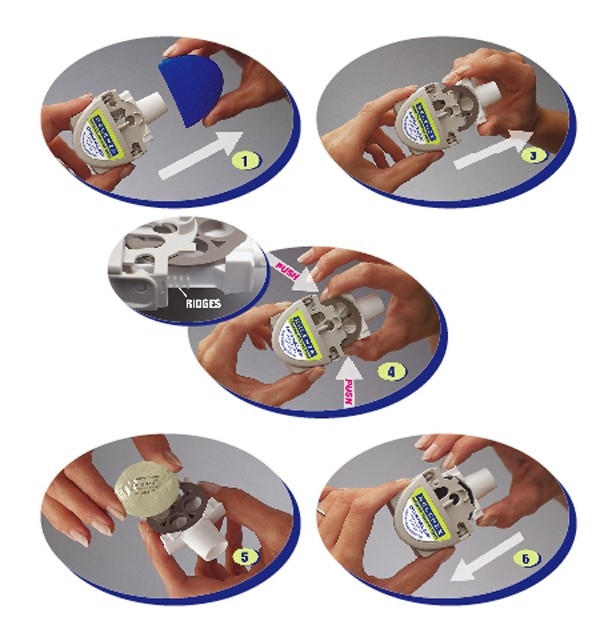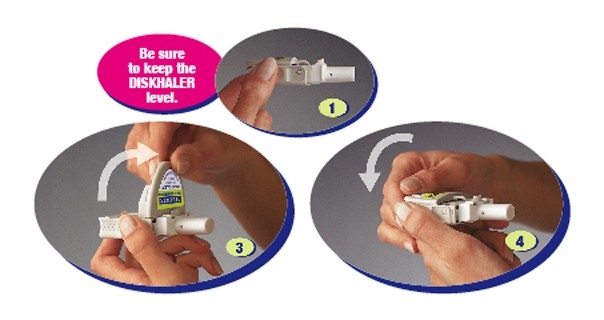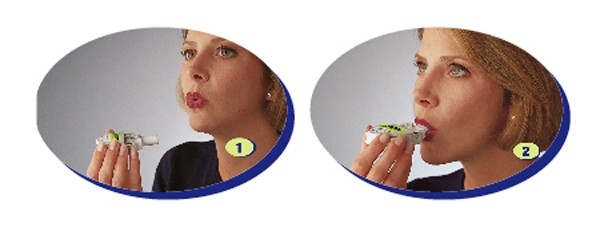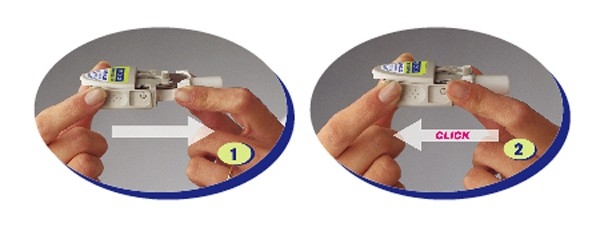 DRUG LABEL: RELENZA
NDC: 68258-3030 | Form: POWDER
Manufacturer: Dispensing Solutions Inc.
Category: prescription | Type: HUMAN PRESCRIPTION DRUG LABEL
Date: 20100302

ACTIVE INGREDIENTS: ZANAMIVIR 5 mg/1 1
INACTIVE INGREDIENTS: LACTOSE

HIGHLIGHTS OF PRESCRIBING INFORMATION

These highlights do not include all the information needed to use RELENZA safely and effectively. See full prescribing information for RELENZA.
RELENZA (zanamivir) Inhalation Powder, for oral inhalation
Initial U.S. Approval: 1999

RECENT MAJOR CHANGES

Indications and Usage Important Limitations on Use of RELENZA (1.3) October 2008

1 INDICATIONS AND USAGE

RELENZA, an influenza neuraminidase inhibitor, is indicated for:

Treatment of influenza in patients 7 years of age and older who have been symptomatic for no more than 2 days. (1.1)

Prophylaxis of influenza in patients 5 years of age and older. (1.2)

Important Limitations on Use of RELENZA:

Not recommended for treatment or prophylaxis of influenza in:

- Individuals with underlying airways disease. (5.1)

Not proven effective for:

- Treatment in individuals with underlying airways disease. (1.3)
- Prophylaxis in nursing home residents. (1.3)

Not a substitute for annual influenza vaccination. (1.3)

Consider available information on influenza drug susceptibility patterns and treatment effects when deciding whether to use RELENZA. (1.3)

2 DOSAGE AND ADMINISTRATION

Indication | Dose
Treatment of Influenza (2.2) | 10 mg twice daily for 5 days
Prophylaxis: (2.3)
Household Setting | 10 mg once daily for 10 days
Community Outbreaks | 10 mg once daily for 28 days

Note: The 10 mg dose is provided by 2 inhalations (one 5 mg blister per inhalation). (2.1)

3 DOSAGE FORMS AND STRENGTHS

Blister for oral inhalation: 5 mg. Four 5 mg blisters of powder on a ROTADISK® for oral inhalation via DISKHALER®. Packaged in carton containing 5 ROTADISKs (total of 10 doses) and 1 DISKHALER inhalation device. (3)

4 CONTRAINDICATIONS

Do not use in patients with history of allergic reaction to any ingredient of RELENZA, including lactose (which contains milk proteins). (4)

5 WARNINGS AND PRECAUTIONS

- Bronchospasm: Serious, sometimes fatal, cases have occurred. Not recommended in individuals with underlying airways disease. Discontinue RELENZA if bronchospasm or decline in respiratory function develops. (5.1)
- Allergic Reactions: Discontinue RELENZA and initiate appropriate treatment if an allergic reaction occurs or is suspected. (5.2)
- Neuropsychiatric Events: Patients with influenza, particularly pediatric patients, may be at an increased risk of seizures, confusion, or abnormal behavior early in their illness. Monitor for signs of abnormal behavior. (5.3)
- High-risk Underlying Medical Conditions: Safety and effectiveness have not been demonstrated in these patients. (5.4)

6 ADVERSE REACTIONS

The most common adverse events reported in >1.5% of patients treated with RELENZA and more commonly than in patients treated with placebo are:

- Treatment Studies – sinusitis, dizziness.
- Prophylaxis Studies – fever and/or chills, arthralgia and articular rheumatism. (6.1)
  To report SUSPECTED ADVERSE REACTIONS, contact GlaxoSmithKline at 1-888-825-5249 or FDA at 1-800-FDA-1088 or www.fda.gov/medwatch.

7 DRUG INTERACTIONS

Live attenuated influenza vaccine, intranasal (7):

- Do not administer until 48 hours following cessation of RELENZA.
- Do not administer RELENZA until 2 weeks following administration of the live attenuated influenza vaccine, unless medically indicated.

Revised: September 2009
RLZ:6PI

FULL PRESCRIBING INFORMATION

1 INDICATIONS AND USAGE

1.1 Treatment of Influenza

RELENZA® (zanamivir) Inhalation Powder is indicated for treatment of uncomplicated acute illness due to influenza A and B virus in adults and pediatric patients 7 years of age and older who have been symptomatic for no more than 2 days.

1.2 Prophylaxis of Influenza

RELENZA is indicated for prophylaxis of influenza in adults and pediatric patients 5 years of age and older.

1.3 Important Limitations on Use of RELENZA

- RELENZA is not recommended for treatment or prophylaxis of influenza in individuals with underlying airways disease (such as asthma or chronic obstructive pulmonary disease) due to risk of serious bronchospasm [see Warnings and Precautions (5.1)].
- RELENZA has not been proven effective for treatment of influenza in individuals with underlying airways disease.
- RELENZA has not been proven effective for prophylaxis of influenza in the nursing home setting.
- RELENZA is not a substitute for early influenza vaccination on an annual basis as recommended by the Centers for Disease Control's Immunization Practices Advisory Committee.
- Influenza viruses change over time. Emergence of resistance mutations could decrease drug effectiveness. Other factors (for example, changes in viral virulence) might also diminish clinical benefit of antiviral drugs. Prescribers should consider available information on influenza drug susceptibility patterns and treatment effects when deciding whether to use RELENZA.
- There is no evidence for efficacy of zanamivir in any illness caused by agents other than influenza virus A and B.
- Patients should be advised that the use of RELENZA for treatment of influenza has not been shown to reduce the risk of transmission of influenza to others.

2 DOSAGE AND ADMINISTRATION

2.1 Dosing Considerations

- RELENZA is for administration to the respiratory tract by oral inhalation only, using the DISKHALER device provided.
- The 10 mg dose is provided by 2 inhalations (one 5 mg blister per inhalation).
- Patients should be instructed in the use of the delivery system. Instructions should include a demonstration whenever possible. If RELENZA is prescribed for children, it should be used only under adult supervision and instruction, and the supervising adult should first be instructed by a healthcare professional [see Patient Counseling Information (17.4)].
- Patients scheduled to use an inhaled bronchodilator at the same time as RELENZA should use their bronchodilator before taking RELENZA [see Patient Counseling Information (17.2)].

2.2 Treatment of Influenza

- The recommended dose of RELENZA for treatment of influenza in adults and pediatric patients 7 years of age and older is 10 mg twice daily (approximately 12 hours apart) for 5 days.
- Two doses should be taken on the first day of treatment whenever possible provided there is at least 2 hours between doses.
- On subsequent days, doses should be about 12 hours apart (e.g., morning and evening) at approximately the same time each day.
- The safety and efficacy of repeated treatment courses have not been studied.

2.3 Prophylaxis of Influenza

Household Setting:

- The recommended dose of RELENZA for prophylaxis of influenza in adults and pediatric patients 5 years of age and older in a household setting is 10 mg once daily for 10 days.
- The dose should be administered at approximately the same time each day.
- There are no data on the effectiveness of prophylaxis with RELENZA in a household setting when initiated more than 1.5 days after the onset of signs or symptoms in the index case.

Community Outbreaks:

- The recommended dose of RELENZA for prophylaxis of influenza in adults and adolescents in a community setting is 10 mg once daily for 28 days.
- The dose should be administered at approximately the same time each day.
- There are no data on the effectiveness of prophylaxis with RELENZA in a community outbreak when initiated more than 5 days after the outbreak was identified in the community.
- The safety and effectiveness of prophylaxis with RELENZA have not been evaluated for longer than 28 days’ duration.

3 DOSAGE FORMS AND STRENGTHS

Blister for oral inhalation: 5 mg. Four 5 mg blisters of powder on a ROTADISK for oral inhalation via DISKHALER. Packaged in carton containing 5 ROTADISKs (total of 10 doses) and 1 DISKHALER inhalation device [see How Supplied/Storage and Handling (16)].

4 CONTRAINDICATIONS

Do not use in patients with history of allergic reaction to any ingredient of RELENZA including lactose (which contains milk proteins) [see Warnings and Precautions (5.2), Description (11)].

5 WARNINGS AND PRECAUTIONS

5.1 Bronchospasm

RELENZA is not recommended for treatment or prophylaxis of influenza in individuals with underlying airways disease (such as asthma or chronic obstructive pulmonary disease).

Serious cases of bronchospasm, including fatalities, have been reported during treatment with RELENZA in patients with and without underlying airways disease. Many of these cases were reported during postmarketing and causality was difficult to assess.

RELENZA should be discontinued in any patient who develops bronchospasm or decline in respiratory function; immediate treatment and hospitalization may be required.

Some patients without prior pulmonary disease may also have respiratory abnormalities from acute respiratory infection that could resemble adverse drug reactions or increase patient vulnerability to adverse drug reactions.

Bronchospasm was documented following administration of zanamivir in 1 of 13 patients with mild or moderate asthma (but without acute influenza-like illness) in a Phase I study. In a Phase III study in patients with acute influenza-like illness superimposed on underlying asthma or chronic obstructive pulmonary disease, 10% (24 of 244) of patients on zanamivir and 9% (22 of 237) on placebo experienced a greater than 20% decline in FEV1 following treatment for 5 days.

If use of RELENZA is considered for a patient with underlying airways disease, the potential risks and benefits should be carefully weighed. If a decision is made to prescribe RELENZA for such a patient, this should be done only under conditions of careful monitoring of respiratory function, close observation, and appropriate supportive care including availability of fast-acting bronchodilators.

5.2 Allergic Reactions

Allergic-like reactions, including oropharyngeal edema, serious skin rashes, and anaphylaxis have been reported in postmarketing experience with RELENZA. RELENZA should be stopped and appropriate treatment instituted if an allergic reaction occurs or is suspected.

5.3 Neuropsychiatric Events

Influenza can be associated with a variety of neurologic and behavioral symptoms which can include events such as seizures, hallucinations, delirium, and abnormal behavior, in some cases resulting in fatal outcomes. These events may occur in the setting of encephalitis or encephalopathy but can occur without obvious severe disease.

There have been postmarketing reports (mostly from Japan) of delirium and abnormal behavior leading to injury in patients with influenza who were receiving neuraminidase inhibitors, including RELENZA. Because these events were reported voluntarily during clinical practice, estimates of frequency cannot be made, but they appear to be uncommon based on usage data for RELENZA. These events were reported primarily among pediatric patients and often had an abrupt onset and rapid resolution. The contribution of RELENZA to these events has not been established. Patients with influenza should be closely monitored for signs of abnormal behavior. If neuropsychiatric symptoms occur, the risks and benefits of continuing treatment should be evaluated for each patient.

5.4 Limitations of Populations Studied

Safety and efficacy have not been demonstrated in patients with high-risk underlying medical conditions. No information is available regarding treatment of influenza in patients with any medical condition sufficiently severe or unstable to be considered at imminent risk of requiring inpatient management.

5.5 Bacterial Infections

Serious bacterial infections may begin with influenza-like symptoms or may coexist with or occur as complications during the course of influenza. RELENZA has not been shown to prevent such complications.

5.6 Importance of Proper Use of DISKHALER

Effective and safe use of RELENZA requires proper use of the DISKHALER to inhale the drug. Prescribers should carefully evaluate the ability of young children to use the delivery system if use of RELENZA is considered [see Use in Specific Populations (8.4)].

6 ADVERSE REACTIONS

See Warnings and Precautions for information about risk of serious adverse events such as bronchospasm (5.1) and allergic-like reactions (5.2), and for safety information in patients with underlying airways disease (5.1).

6.1 Clinical Trials Experience

Because clinical trials are conducted under widely varying conditions, adverse reaction rates observed in the clinical trials of a drug cannot be directly compared with rates in the clinical trials of another drug and may not reflect the rates observed in practice.

The placebo used in clinical studies consisted of inhaled lactose powder, which is also the vehicle for the active drug; therefore, some adverse events occurring at similar frequencies in different treatment groups could be related to lactose vehicle inhalation.

Treatment of Influenza: Clinical Trials in Adults and Adolescents: Adverse events that occurred with an incidence ≥1.5% in treatment studies are listed in Table 1. This table shows adverse events occurring in patients ≥12 years of age receiving RELENZA 10 mg inhaled twice daily, RELENZA in all inhalation regimens, and placebo inhaled twice daily (where placebo consisted of the same lactose vehicle used in RELENZA).

Table 1. Summary of Adverse Events ≥1.5% Incidence During Treatment in Adults and Adolescents
Adverse Event | RELENZA |  | Placebo; (Lactose Vehicle); (n = 1,520)
Adverse Event | 10 mg b.i.d. Inhaled; (n = 1,132) | All Dosing Regimensa; (n = 2,289) | Placebo; (Lactose Vehicle); (n = 1,520)
Body as a whole
Headaches | 2% | 2% | 3%
Digestive
Diarrhea | 3% | 3% | 4%
Nausea | 3% | 3% | 3%
Vomiting | 1% | 1% | 2%
Respiratory
Nasal signs and symptoms | 2% | 3% | 3%
Bronchitis | 2% | 2% | 3%
Cough | 2% | 2% | 3%
Sinusitis | 3% | 2% | 2%
Ear, nose, and throat infections | 2% | 1% | 2%
Nervous system
Dizziness | 2% | 1% | <1%
a Includes studies where RELENZA was administered intranasally (6.4 mg 2 to 4 times per day in addition to inhaled preparation) and/or inhaled more frequently (q.i.d.) than the currently recommended dose.

Additional adverse reactions occurring in less than 1.5% of patients receiving RELENZA included malaise, fatigue, fever, abdominal pain, myalgia, arthralgia, and urticaria.

The most frequent laboratory abnormalities in Phase III treatment studies included elevations of liver enzymes and CPK, lymphopenia, and neutropenia. These were reported in similar proportions of zanamivir and lactose vehicle placebo recipients with acute influenza-like illness.

Clinical Trials in Pediatric Patients: Adverse events that occurred with an incidence ≥1.5% in children receiving treatment doses of RELENZA in 2 Phase III studies are listed in Table 2. This table shows adverse events occurring in pediatric patients 5 to 12 years old receiving RELENZA 10 mg inhaled twice daily and placebo inhaled twice daily (where placebo consisted of the same lactose vehicle used in RELENZA).

Table 2. Summary of Adverse Events ≥1.5% Incidence During Treatment in Pediatric Patientsa
Adverse Event | RELENZA; 10 mg b.i.d. Inhaled; (n = 291) | Placebo; (Lactose Vehicle); (n = 318)
Respiratory
Ear, nose, and throat infections | 5% | 5%
Ear, nose, and throat hemorrhage | <1% | 2%
Asthma | <1% | 2%
Cough | <1% | 2%
Digestive
Vomiting | 2% | 3%
Diarrhea | 2% | 2%
Nausea | <1% | 2%
a Includes a subset of patients receiving RELENZA for treatment of influenza in a prophylaxis study.

In 1 of the 2 studies described in Table 2, some additional information is available from children (5 to 12 years old) without acute influenza-like illness who received an investigational prophylaxis regimen of RELENZA; 132 children received RELENZA and 145 children received placebo. Among these children, nasal signs and symptoms (zanamivir 20%, placebo 9%), cough (zanamivir 16%, placebo 8%), and throat/tonsil discomfort and pain (zanamivir 11%, placebo 6%) were reported more frequently with RELENZA than placebo. In a subset with chronic pulmonary disease, lower respiratory adverse events (described as asthma, cough, or viral respiratory infections which could include influenza-like symptoms) were reported in 7 of 7 zanamivir recipients and 5 of 12 placebo recipients.

Prophylaxis of Influenza: Family/Household Prophylaxis Studies: Adverse events that occurred with an incidence of ≥1.5% in the 2 prophylaxis studies are listed in Table 3. This table shows adverse events occurring in patients ≥5 years of age receiving RELENZA 10 mg inhaled once daily for 10 days.

Table 3. Summary of Adverse Events ≥1.5% Incidence During 10-Day Prophylaxis Studies in Adults, Adolescents, and Childrena
Adverse Event | Contact Cases
Adverse Event | RELENZA; (n = 1,068) | Placebo; (n = 1,059)
Lower respiratory
Viral respiratory infections | 13% | 19%
Cough | 7% | 9%
Neurologic
Headaches | 13% | 14%
Ear, nose, and throat
Nasal signs and symptoms | 12% | 12%
Throat and tonsil discomfort and pain | 8% | 9%
Nasal inflammation | 1% | 2%
Musculoskeletal
Muscle pain | 3% | 3%
Endocrine and metabolic
Feeding problems (decreased or increased appetite and anorexia) | 2% | 2%
Gastrointestinal
Nausea and vomiting | 1% | 2%
Non-site specific
Malaise and fatigue | 5% | 5%
Temperature regulation disturbances (fever and/or chills) | 5% | 4%
a In prophylaxis studies, symptoms associated with influenza-like illness were captured as adverse events; subjects were enrolled during a winter respiratory season during which time any symptoms that occurred were captured as adverse events.

Community Prophylaxis Studies: Adverse events that occurred with an incidence of ≥1.5% in 2 prophylaxis studies are listed in Table 4. This table shows adverse events occurring in patients ≥5 years of age receiving RELENZA 10 mg inhaled once daily for 28 days.

Table 4. Summary of Adverse Events ≥1.5% Incidence During 28-Day Prophylaxis Studies in Adults, Adolescents, and Childrena
Adverse Event | RELENZA; (n = 2,231) | Placebo; (n = 2,239)
Neurologic
Headaches | 24% | 26%
Ear, nose, and throat
Throat and tonsil discomfort and pain | 19% | 20%
Nasal signs and symptoms | 12% | 13%
Ear, nose, and throat infections | 2% | 2%
Lower respiratory
Cough | 17% | 18%
Viral respiratory infections | 3% | 4%
Musculoskeletal
Muscle pain | 8% | 8%
Musculoskeletal pain | 6% | 6%
Arthralgia and articular rheumatism | 2% | <1%
Endocrine and metabolic
Feeding problems (decreased or increased appetite and anorexia) | 4% | 4%
Gastrointestinal
Nausea and vomiting | 2% | 3%
Diarrhea | 2% | 2%
Non-site specific
Temperature regulation disturbances (fever and/or chills) | 9% | 10%
Malaise and fatigue | 8% | 8%
a In prophylaxis studies, symptoms associated with influenza-like illness were captured as adverse events; subjects were enrolled during a winter respiratory season during which time any symptoms that occurred were captured as adverse events.

6.2 Postmarketing Experience

In addition to adverse events reported from clinical trials, the following events have been identified during postmarketing use of zanamivir (RELENZA). Because they are reported voluntarily from a population of unknown size, estimates of frequency cannot be made. These events have been chosen for inclusion due to a combination of their seriousness, frequency of reporting, or potential causal connection to zanamivir (RELENZA).

Allergic Reactions: Allergic or allergic-like reaction, including oropharyngeal edema [see Warnings and Precautions (5.2)].

Psychiatric: Delirium, including symptoms such as altered level of consciousness, confusion, abnormal behavior, delusions, hallucinations, agitation, anxiety, nightmares[see Warnings and Precautions (5.3)].

Cardiac: Arrhythmias, syncope.

Neurologic: Seizures.

Respiratory: Bronchospasm, dyspnea [see Warnings and Precautions (5.1)].

Skin: Facial edema; rash, including serious cutaneous reactions (e.g., erythema multiforme, Stevens-Johnson syndrome, toxic epidermal necrolysis); urticaria [see Warnings and Precautions (5.2)].

7 DRUG INTERACTIONS

Zanamivir is not a substrate nor does it affect cytochrome P450 (CYP) isoenzymes (CYP1A1/2, 2A6, 2C9, 2C18, 2D6, 2E1, and 3A4) in human liver microsomes. No clinically significant pharmacokinetic drug interactions are predicted based on data from in vitro studies.

The concurrent use of RELENZA with live attenuated influenza vaccine (LAIV) intranasal has not been evaluated. However, because of potential interference between these products, LAIV should not be administered within 2 weeks before or 48 hours after administration of RELENZA, unless medically indicated. The concern about possible interference arises from the potential for antiviral drugs to inhibit replication of live vaccine virus.

Trivalent inactivated influenza vaccine can be administered at any time relative to use of RELENZA [see Clinical Pharmacology (12.4)].

8 USE IN SPECIFIC POPULATIONS

8.1 Pregnancy

Pregnancy Category C. There are no adequate and well-controlled studies of zanamivir in pregnant women. Zanamivir should be used during pregnancy only if the potential benefit justifies the potential risk to the fetus.

Embryo/fetal development studies were conducted in rats (dosed from days 6 to 15 of pregnancy) and rabbits (dosed from days 7 to 19 of pregnancy) using the same IV doses (1, 9, and 90 mg/kg/day). Pre- and post-natal developmental studies were performed in rats (dosed from day 16 of pregnancy until litter day 21 to 23). No malformations, maternal toxicity, or embryotoxicity were observed in pregnant rats or rabbits and their fetuses. Because of insufficient blood sampling timepoints in rat and rabbit reproductive toxicity studies, AUC values were not available. In a subchronic study in rats at the 90 mg/kg/day IV dose, the AUC values were greater than 300 times the human exposure at the proposed clinical dose.

An additional embryo/fetal study, in a different strain of rat, was conducted using subcutaneous administration of zanamivir, 3 times daily, at doses of 1, 9, or 80 mg/kg during days 7 to 17 of pregnancy. There was an increase in the incidence rates of a variety of minor skeleton alterations and variants in the exposed offspring in this study. Based on AUC measurements, the 80 mg/kg dose produced an exposure greater than 1,000 times the human exposure at the proposed clinical dose. However, in most instances, the individual incidence rate of each skeletal alteration or variant remained within the background rates of the historical occurrence in the strain studied.

Zanamivir has been shown to cross the placenta in rats and rabbits. In these animals, fetal blood concentrations of zanamivir were significantly lower than zanamivir concentrations in the maternal blood.

8.3 Nursing Mothers

Studies in rats have demonstrated that zanamivir is excreted in milk. However, nursing mothers should be instructed that it is not known whether zanamivir is excreted in human milk. Because many drugs are excreted in human milk, caution should be exercised when RELENZA is administered to a nursing mother.

8.4 Pediatric Use

Treatment of Influenza: Safety and effectiveness of RELENZA for treatment of influenza have not been assessed in pediatric patients less than 7 years of age, but were studied in a Phase III treatment study in pediatric patients, where 471 children 5 to 12 years of age received zanamivir or placebo [see Clinical Studies 14.1)]. Adolescents were included in the 3 principal Phase III adult treatment studies. In these studies, 67 patients were 12 to 16 years of age. No definite differences in safety and efficacy were observed between these adolescent patients and young adults.

In a Phase I study of 16 children ages 6 to 12 years with signs and symptoms of respiratory disease, 4 did not produce a measurable peak inspiratory flow rate (PIFR) through the DISKHALER (3 with no adequate inhalation on request, 1 with missing data), 9 had measurable PIFR on each of 2 inhalations, and 3 achieved measurable PIFR on only 1 of 2 inhalations. Neither of two 6-year-olds and one of two 7-year-olds produced measurable PIFR. Overall, 8 of the 16 children (including all those under 8 years old) either did not produce measurable inspiratory flow through the DISKHALER or produced peak inspiratory flow rates below the 60 L/min considered optimal for the device under standardized in vitro testing; lack of measurable flow rate was related to low or undetectable serum concentrations [see Clinical Pharmacology (12.3), Clinical Studies (14.1)]. Prescribers should carefully evaluate the ability of young children to use the delivery system if prescription of RELENZA is considered.

Prophylaxis of Influenza: The safety and effectiveness of RELENZA for prophylaxis of influenza have been studied in 4 Phase III studies where 273 children 5 to 11 years of age and 239 adolescents 12 to 16 years of age received RELENZA. No differences in safety and effectiveness were observed between pediatric and adult subjects [see Clinical Studies (14.2)].

8.5 Geriatric Use

Of the total number of patients in 6 clinical studies of RELENZA for treatment of influenza, 59 patients were 65 years of age and older, while 24 patients were 75 years of age and older. Of the total number of patients in 4 clinical studies of RELENZA for prophylaxis of influenza in households and community settings, 954 patients were 65 years of age and older, while 347 patients were 75 years of age and older. No overall differences in safety or effectiveness were observed between these patients and younger patients, and other reported clinical experience has not identified differences in responses between the elderly and younger patients, but greater sensitivity of some older individuals cannot be ruled out. Elderly patients may need assistance with use of the device.

In 2 additional studies of RELENZA for prophylaxis of influenza in the nursing home setting, efficacy was not demonstrated [see Indications and Usage (1.3)].

10 OVERDOSAGE

There have been no reports of overdosage from administration of RELENZA.

11 DESCRIPTION

The active component of RELENZA is zanamivir. The chemical name of zanamivir is 5-(acetylamino)-4-[(aminoiminomethyl)-amino]-2,6-anhydro-3,4,5-trideoxy-D-glycero-D-galacto-non-2-enonic acid. It has a molecular formula of C12H20N4O7 and a molecular weight of 332.3. It has the following structural formula:

Zanamivir is a white to off-white powder for oral inhalation with a solubility of approximately 18 mg/mL in water at 20°C.

RELENZA is for administration to the respiratory tract by oral inhalation only. Each RELENZA ROTADISK contains 4 regularly spaced double-foil blisters with each blister containing a powder mixture of 5 mg of zanamivir and 20 mg of lactose (which contains milk proteins). The contents of each blister are inhaled using a specially designed breath-activated plastic device for inhaling powder called the DISKHALER. After a RELENZA ROTADISK is loaded into the DISKHALER, a blister that contains medication is pierced and the zanamivir is dispersed into the air stream created when the patient inhales through the mouthpiece. The amount of drug delivered to the respiratory tract will depend on patient factors such as inspiratory flow. Under standardized in vitro testing, RELENZA ROTADISK delivers 4 mg of zanamivir from the DISKHALER device when tested at a pressure drop of 3 kPa (corresponding to a flow rate of about 62 to 65 L/min) for 3 seconds.

12 CLINICAL PHARMACOLOGY

12.1 Mechanism of Action

Zanamivir is an antiviral drug [see Clinical Pharmacology (12.4)].

12.3 Pharmacokinetics

Absorption and Bioavailability: Pharmacokinetic studies of orally inhaled zanamivir indicate that approximately 4% to 17% of the inhaled dose is systemically absorbed. The peak serum concentrations ranged from 17 to 142 ng/mL within 1 to 2 hours following a 10 mg dose. The area under the serum concentration versus time curve (AUC∞) ranged from 111 to 1,364 ng•hr/mL.

Distribution: Zanamivir has limited plasma protein binding (<10%).

Metabolism: Zanamivir is renally excreted as unchanged drug. No metabolites have been detected in humans.

Elimination: The serum half-life of zanamivir following administration by oral inhalation ranges from 2.5 to 5.1 hours. It is excreted unchanged in the urine with excretion of a single dose completed within 24 hours. Total clearance ranges from 2.5 to 10.9 L/hr. Unabsorbed drug is excreted in the feces.

Impaired Hepatic Function: The pharmacokinetics of zanamivir have not been studied in patients with impaired hepatic function.

Impaired Renal Function: After a single intravenous dose of 4 mg or 2 mg of zanamivir in volunteers with mild/moderate or severe renal impairment, respectively, significant decreases in renal clearance (and hence total clearance: normals 5.3 L/hr, mild/moderate 2.7 L/hr, and severe 0.8 L/hr; median values) and significant increases in half-life (normals 3.1 hr, mild/moderate 4.7 hr, and severe 18.5 hr; median values) and systemic exposure were observed. Safety and efficacy have not been documented in the presence of severe renal insufficiency. Due to the low systemic bioavailability of zanamivir following oral inhalation, no dosage adjustments are necessary in patients with renal impairment. However, the potential for drug accumulation should be considered.

Pediatric Patients: The pharmacokinetics of zanamivir were evaluated in pediatric patients with signs and symptoms of respiratory illness. Sixteen patients, 6 to 12 years of age, received a single dose of 10 mg zanamivir dry powder via DISKHALER. Five patients had either undetectable zanamivir serum concentrations or had low drug concentrations (8.32 to 10.38 ng/mL) that were not detectable after 1.5 hours. Eleven patients had Cmax median values of 43 ng/mL (range 15 to 74) and AUC∞ median values of 167 ng•hr/mL (range 58 to 279). Low or undetectable serum concentrations were related to lack of measurable PIFR in individual patients [see Use in Specific Populations (8.4), Clinical Studies (14.1)].

Geriatric Patients: The pharmacokinetics of zanamivir have not been studied in patients over 65 years of age [see Use in Specific Populations (8.5)].

Gender, Race, and Weight: In a population pharmacokinetic analysis in patient studies, no clinically significant differences in serum concentrations and/or pharmacokinetic parameters (V/F, CL/F, ka, AUC0-3, Cmax, Tmax, CLr, and % excreted in urine) were observed when demographic variables (gender, age, race, and weight) and indices of infection (laboratory evidence of infection, overall symptoms, symptoms of upper respiratory illness, and viral titers) were considered. There were no significant correlations between measures of systemic exposure and safety parameters.

12.4 Microbiology

Mechanism of Action: Zanamivir is an inhibitor of influenza virus neuraminidase affecting release of viral particles.

Antiviral Activity: The antiviral activity of zanamivir against laboratory and clinical isolates of influenza virus was determined in cell culture assays. The concentrations of zanamivir required for inhibition of influenza virus were highly variable depending on the assay method used and virus isolate tested. The 50% and 90% effective concentrations (EC50 and EC90) of zanamivir were in the range of 0.005 to 16.0 μM and 0.05 to >100 μM, respectively (1 μM = 0.33 mcg/mL). The relationship between the cell culture inhibition of influenza virus by zanamivir and the inhibition of influenza virus replication in humans has not been established.

Resistance: Influenza viruses with reduced susceptibility to zanamivir have been selected in cell culture by multiple passages of the virus in the presence of increasing concentrations of the drug. Genetic analysis of these viruses showed that the reduced susceptibility in cell culture to zanamivir is associated with mutations that result in amino acid changes in the viral neuraminidase or viral hemagglutinin or both. Resistance mutations selected in cell culture which result in neuraminidase amino acid substitutions include E119G/A/D and R292K. Mutations selected in cell culture in hemagglutinin include: K68R, G75E, E114K, N145S, S165N, S186F, N199S, and K222T.

In an immunocompromised patient infected with influenza B virus, a variant virus emerged after treatment with an investigational nebulized solution of zanamivir for 2 weeks. Analysis of this variant showed a hemagglutinin substitution (T198I) which resulted in a reduced affinity for human cell receptors, and a substitution in the neuraminidase active site (R152K) which reduced the enzyme’s activity to zanamivir by 1,000-fold. Insufficient information is available to characterize the risk of emergence of zanamivir resistance in clinical use.

Cross-Resistance: Cross-resistance has been observed between some zanamivir-resistant and some oseltamivir-resistant influenza virus mutants generated in cell culture. However, some of the in cell culture zanamivir-induced resistance mutations, E119G/A/D and R292K, occurred at the same neuraminidase amino acid positions as in the clinical isolates resistant to oseltamivir, E119V and R292K. No studies have been performed to assess risk of emergence of cross-resistance during clinical use.

Influenza Vaccine Interaction Study: An interaction study (n = 138) was conducted to evaluate the effects of zanamivir (10 mg once daily) on the serological response to a single dose of trivalent inactivated influenza vaccine, as measured by hemagglutination inhibition titers. There was no difference in hemagglutination inhibition antibody titers at 2 weeks and 4 weeks after vaccine administration between zanamivir and placebo recipients.

Influenza Challenge Studies: Antiviral activity of zanamivir was supported for infection with influenza A virus, and to a more limited extent for infection with influenza B virus, by Phase I studies in volunteers who received intranasal inoculations of challenge strains of influenza virus, and received an intranasal formulation of zanamivir or placebo starting before or shortly after viral inoculation.

13 NONCLINICAL TOXICOLOGY

13.1 Carcinogenesis, Mutagenesis, Impairment of Fertility

Carcinogenesis: In 2-year carcinogenicity studies conducted in rats and mice using a powder formulation administered through inhalation, zanamivir induced no statistically significant increases in tumors over controls. The maximum daily exposures in rats and mice were approximately 23 to 25 and 20 to 22 times, respectively, greater than those in humans at the proposed clinical dose based on AUC comparisons.

Mutagenesis: Zanamivir was not mutagenic in in vitro and in vivo genotoxicity assays which included bacterial mutation assays in S. typhimurium and E. coli, mammalian mutation assays in mouse lymphoma, chromosomal aberration assays in human peripheral blood lymphocytes, and the in vivo mouse bone marrow micronucleus assay.

Impairment of Fertility: The effects of zanamivir on fertility and general reproductive performance were investigated in male (dosed for 10 weeks prior to mating, and throughout mating, gestation/lactation, and shortly after weaning) and female rats (dosed for 3 weeks prior to mating through Day 19 of pregnancy, or Day 21 post partum) at IV doses 1, 9, and 90 mg/kg/day. Zanamivir did not impair mating or fertility of male or female rats, and did not affect the sperm of treated male rats. The reproductive performance of the F1 generation born to female rats given zanamivir was not affected. Based on a subchronic study in rats at a 90 mg/kg/day IV dose, AUC values ranged between 142 and 199 mcg•hr/mL (>300 times the human exposure at the proposed clinical dose).

14 CLINICAL STUDIES

14.1 Treatment of Influenza

Adults and Adolescents: The efficacy of RELENZA 10 mg inhaled twice daily for 5 days in the treatment of influenza has been evaluated in placebo-controlled studies conducted in North America, the Southern Hemisphere, and Europe during their respective influenza seasons. The magnitude of treatment effect varied between studies, with possible relationships to population-related factors including amount of symptomatic relief medication used.

Populations Studied: The principal Phase III studies enrolled 1,588 patients ages 12 years and older (median age 34 years, 49% male, 91% Caucasian), with uncomplicated influenza-like illness within 2 days of symptom onset. Influenza was confirmed by culture, hemagglutination inhibition antibodies, or investigational direct tests. Of 1,164 patients with confirmed influenza, 89% had influenza A and 11% had influenza B. These studies served as the principal basis for efficacy evaluation, with more limited Phase II studies providing supporting information where necessary. Following randomization to either zanamivir or placebo (inhaled lactose vehicle), all patients received instruction and supervision by a healthcare professional for the initial dose.

Principal Results: The definition of time to improvement in major symptoms of influenza included no fever and self-assessment of “none” or “mild” for headache, myalgia, cough, and sore throat. A Phase II and a Phase III study conducted in North America (total of over 600 influenza-positive patients) suggested up to 1 day of shortening of median time to this defined improvement in symptoms in patients receiving zanamivir compared with placebo, although statistical significance was not reached in either of these studies. In a study conducted in the Southern Hemisphere (321 influenza-positive patients), a 1.5-day difference in median time to symptom improvement was observed. Additional evidence of efficacy was provided by the European study.

Other Findings: There was no consistent difference in treatment effect in patients with influenza A compared with influenza B; however, these trials enrolled smaller numbers of patients with influenza B and thus provided less evidence in support of efficacy in influenza B.

In general, patients with lower temperature (e.g., 38.2°C or less) or investigator-rated as having less severe symptoms at entry derived less benefit from therapy.

No consistent treatment effect was demonstrated in patients with underlying chronic medical conditions, including respiratory or cardiovascular disease [see Warnings and Precautions (5.4)].

No consistent differences in rate of development of complications were observed between treatment groups.

Some fluctuation of symptoms was observed after the primary study endpoint in both treatment groups.

Pediatric Patients: The efficacy of RELENZA 10 mg inhaled twice daily for 5 days in the treatment of influenza in pediatric patients has been evaluated in a placebo-controlled study conducted in North America and Europe, enrolling 471 patients, ages 5 to 12 years (55% male, 90% Caucasian), within 36 hours of symptom onset. Of 346 patients with confirmed influenza, 65% had influenza A and 35% had influenza B. The definition of time to improvement included no fever and parental assessment of no or mild cough and absent/minimal muscle and joint aches or pains, sore throat, chills/feverishness, and headache. Median time to symptom improvement was 1 day shorter in patients receiving zanamivir compared with placebo. No consistent differences in rate of development of complications were observed between treatment groups. Some fluctuation of symptoms was observed after the primary study endpoint in both treatment groups.

Although this study was designed to enroll children ages 5 to 12 years, the product is indicated only for children 7 years of age and older. This evaluation is based on the combination of lower estimates of treatment effect in 5- and 6-year-olds compared with the overall study population, and evidence of inadequate inhalation through the DISKHALER in a pharmacokinetic study [see Use in Specific Populations (8.4), Clinical Pharmacology (12.3)].

14.2 Prophylaxis of Influenza

The efficacy of RELENZA in preventing naturally occurring influenza illness has been demonstrated in 2 post-exposure prophylaxis studies in households and 2 seasonal prophylaxis studies during community outbreaks of influenza. The primary efficacy endpoint in these studies was the incidence of symptomatic, laboratory-confirmed influenza, defined as the presence of 2 or more of the following symptoms: oral temperature ≥100°F/37.8°C or feverishness, cough, headache, sore throat, and myalgia; and laboratory confirmation of influenza A or B by culture, PCR, or seroconversion (defined as a 4-fold increase in convalescent antibody titer from baseline).

Household Prophylaxis Studies: Two studies assessed post-exposure prophylaxis in household contacts of an index case. Within 1.5 days of onset of symptoms in an index case, each household (including all family members ≥5 years of age) was randomized to RELENZA 10 mg inhaled once daily or placebo inhaled once daily for 10 days. In the first study only, each index case was randomized to RELENZA 10 mg inhaled twice daily for 5 days or inhaled placebo twice daily for 5 days. In this study, the proportion of households with at least 1 new case of symptomatic laboratory-confirmed influenza was reduced from 19.0% (32 of 168 households) for the placebo group to 4.1% (7 of 169 households) for the group receiving RELENZA.

In the second study, index cases were not treated. The incidence of symptomatic laboratory-confirmed influenza was reduced from 19.0% (46 of 242 households) for the placebo group to 4.1% (10 of 245 households) for the group receiving RELENZA.

Seasonal Prophylaxis Studies: Two seasonal prophylaxis studies assessed RELENZA 10 mg inhaled once daily versus placebo inhaled once daily for 28 days during community outbreaks. The first study enrolled subjects 18 years of age or greater (mean age 29 years) from 2 university communities. The majority of subjects were unvaccinated (86%). In this study, the incidence of symptomatic laboratory-confirmed influenza was reduced from 6.1% (34 of 554) for the placebo group to 2.0% (11 of 553) for the group receiving RELENZA.

The second seasonal prophylaxis study enrolled subjects 12 to 94 years of age (mean age 60 years) with 56% of them older than 65 years of age. Sixty-seven percent of the subjects were vaccinated. In this study, the incidence of symptomatic laboratory-confirmed influenza was reduced from 1.4% (23 of 1,685) for the placebo group to 0.2% (4 of 1,678) for the group receiving RELENZA.

16 HOW SUPPLIED/STORAGE AND HANDLING

RELENZA is supplied in a circular double-foil pack (a ROTADISK) containing 4 blisters of the drug. Five ROTADISKs are packaged in a white polypropylene tube. The tube is packaged in a carton with 1 blue and gray DISKHALER inhalation device.

They are supplied by Dispensing Solutions Inc. as follows:

NDC | Strength | Quantity/Form | Source NDC
68258-3030-1 | 5 mg | 5 Rotadisks containing 4 Blisters | 0173-0681-01

This product was Manufactured By:

GlaxoSmithKline
Research Triangle Park, NC 27709
Made in UK

And Relabeled By:

Dispensing Solutions Inc.
3000 West Warner Ave
Santa Ana, CA 92704
United States

Store at 25°C (77°F); excursions permitted to 15° to 30°C (59° to 86°F) (see USP Controlled Room Temperature). Keep out of reach of children. Do not puncture any RELENZA ROTADISK blister until taking a dose using the DISKHALER.

17 PATIENT COUNSELING INFORMATION

See FDA-Approved Patient Labeling provided as a separate leaflet accompanying the product.

17.1 Bronchospasm

Patients should be advised of the risk of bronchospasm, especially in the setting of underlying airways disease, and should stop RELENZA and contact their physician if they experience increased respiratory symptoms during treatment such as worsening wheezing, shortness of breath, or other signs or symptoms of bronchospasm [see Warnings and Precautions (5.1)]. If a decision is made to prescribe RELENZA for a patient with asthma or chronic obstructive pulmonary disease, the patient should be made aware of the risks and should have a fast-acting bronchodilator available.

17.2 Concomitant Bronchodilator Use

Patients scheduled to take inhaled bronchodilators at the same time as RELENZA should be advised to use their bronchodilators before taking RELENZA.

17.3 Neuropsychiatric Events

Patients with influenza (the flu), particularly children and adolescents, may be at an increased risk of seizures, confusion, or abnormal behavior early in their illness. These events may occur after beginning RELENZA or may occur when flu is not treated. These events are uncommon but may result in accidental injury to the patient. Therefore, patients should be observed for signs of unusual behavior and a healthcare professional should be contacted immediately if the patient shows any signs of unusual behavior [see Warnings and Precautions (5.3)].

17. 4 Instructions for Use

Patients should be instructed in use of the delivery system. Instructions should include a demonstration whenever possible. For the proper use of RELENZA, the patient should read and follow carefully the accompanying Patient Instructions for Use.

If RELENZA is prescribed for children, it should be used only under adult supervision and instruction, and the supervising adult should first be instructed by a healthcare professional [see Dosage and Administration (2.1)].

17.5 Risk of Influenza Transmission to Others

Patients should be advised that the use of RELENZA for treatment of influenza has not been shown to reduce the risk of transmission of influenza to others.

RELENZA, DISKHALER, and ROTADISK are registered trademarks of GlaxoSmithKline.

GlaxoSmithKline
Research Triangle Park, NC 27709

©2009, GlaxoSmithKline. All rights reserved.

PATIENT LABELING

RELENZA® (zanamivir) Inhalation Powder

This leaflet contains important patient information about RELENZA (zanamivir) Inhalation Powder, and should be read completely before beginning treatment. It does not, however, take the place of discussions with your healthcare provider about your medical condition or your treatment. This summary does not list all benefits and risks of RELENZA. The medication described here can only be prescribed and dispensed by a licensed healthcare provider, who has information about your medical condition and more information about the drug, including how to take it, what to expect, and potential side effects. If you have any questions about RELENZA, talk with your healthcare provider.

What is RELENZA?

RELENZA (ruh-LENS-uh) is a medicine for the treatment of influenza (flu, infection caused by influenza virus) and for reducing the chance of getting the flu in community and household settings. It belongs to a group of medicines called neuraminidase inhibitors. These medications attack the influenza virus and prevent it from spreading inside your body. RELENZA treats the cause of influenza at its source, rather than simply masking the symptoms.

Important Safety Information About RELENZA

Some patients have had bronchospasm (wheezing) or serious breathing problems when they used RELENZA. Many but not all of these patients had previous asthma or chronic obstructive pulmonary disease. RELENZA has not been shown to shorten the duration of influenza in people with these diseases. Because of the risk of side effects and because it has not been shown to help them, RELENZA is not recommended for people with chronic respiratory disease such as asthma or chronic obstructive pulmonary disease.

If you develop worsening respiratory symptoms such as wheezing or shortness of breath, stop using RELENZA and contact your healthcare provider right away.

If you have chronic respiratory disease such as asthma and chronic obstructive pulmonary disease and your healthcare provider has prescribed RELENZA, you should have a fast-acting, inhaled bronchodilator available for your use. If you are scheduled to use an inhaled bronchodilator at the same time as RELENZA, use the inhaled bronchodilator before using RELENZA.

Read the rest of this leaflet for more information about side effects and risks.

Other kinds of infections can appear like influenza or occur along with influenza, and need different kinds of treatment. Contact your healthcare provider if you feel worse or develop new symptoms during or after treatment, or if your influenza symptoms do not start to get better.

Who should not take RELENZA?

RELENZA is not recommended for people who have chronic lung disease such as asthma or chronic obstructive pulmonary disease. RELENZA has not been shown to shorten the duration of influenza in people with these diseases, and some people have had serious side effects of bronchospasm and worsening lung function. (See the section of this Patient Information entitled “Important Safety Information About RELENZA.”)

You should not take RELENZA if you are allergic to zanamivir or any other ingredient of RELENZA. Also tell your healthcare provider if you have any type of chronic condition including lung or heart disease, if you are allergic to any other medicines or food products, or if you are pregnant.

RELENZA was not effective in reducing the chance of getting the flu in 2 studies in nursing home patients.

RELENZA does not treat flu-like illness that is not caused by influenza virus.

Who should consider taking RELENZA?

Adult and pediatric patients at least 7 years of age who have influenza symptoms that appeared within the previous day or two. Typical symptoms of influenza include sudden onset of fever, cough, headache, fatigue, muscular weakness, and sore throat.

RELENZA can also help reduce the chance of getting the flu in adults and children at least 5 years of age who have a higher chance of getting the flu because they spend time with someone who has the flu. RELENZA can also reduce the chance of getting the flu if there is a flu outbreak in the community.

The use of RELENZA for the treatment of flu has not been shown to reduce the risk of spreading the virus to others.

Can I take other medications with RELENZA?

RELENZA has been shown to have an acceptable safety profile when used as labeled, with minimal risk of drug interactions. Your healthcare provider may recommend taking other medications, including over-the-counter medications, to reduce fever or other symptoms while you are taking RELENZA. Before starting treatment, make sure that your healthcare provider knows if you are taking other medicines. If you are scheduled to use an inhaled bronchodilator at the same time as RELENZA, you should use the inhaled bronchodilator before using RELENZA.

Before taking RELENZA, please let your healthcare provider know if you received live attenuated influenza vaccine (FLUMIST®) intranasal in the past 2 weeks.

How and when should I take RELENZA?

RELENZA is packaged in medicine disks called ROTADISKS® and is inhaled by mouth using a delivery device called a DISKHALER®. Each ROTADISK contains 4 blisters. Each blister contains 5 mg of active drug and 20 mg of lactose powder (which contains milk proteins).

You should receive a demonstration on how to use RELENZA in the DISKHALER from a healthcare provider. Before taking RELENZA, read the “Patient Instructions for Use.” Make sure that you understand these instructions and talk to your healthcare provider if you have any questions. Children who use RELENZA should always be supervised by an adult who understands how to use RELENZA. Proper use of the DISKHALER to inhale the drug is necessary for safe and effective use of RELENZA.

If you have the flu the usual dose for treatment is 2 inhalations of RELENZA (1 blister per inhalation) twice daily (in the morning and evening) for 5 days. It is important that you begin your treatment with RELENZA as soon as possible from the first appearance of your flu symptoms. Take 2 doses on the first day of treatment whenever possible if there are at least 2 hours between doses.

To reduce the chance of getting the flu, the usual dose is 2 inhalations of RELENZA (1 blister per inhalation) once daily for 10 or 28 days as prescribed by your healthcare provider.

Never share RELENZA with anyone, even if they have the same symptoms. If you feel worse or develop new symptoms during treatment with RELENZA, or if your flu symptoms do not start to get better, stop using the medicine and contact your healthcare provider.

What if I miss a dose?

If you forget to take your medicine at any time, take the missed dose as soon as you remember, except if it is near the next dose (within 2 hours). Then continue to take RELENZA at the usual times. You do not need to take a double dose. If you have missed several doses, inform your healthcare provider and follow the advice given to you.

What are important or common possible side effects of taking RELENZA?

Some patients have had breathing problems while taking RELENZA. This can be very serious and need treatment right away. Most of the patients who had this problem had asthma or chronic obstructive pulmonary disease, but some did not. If you have trouble breathing or have wheezing after your dose of RELENZA, stop taking RELENZA and get medical attention.

In studies, the most common side effects with RELENZA have been headaches; diarrhea; nausea; vomiting; nasal irritation; bronchitis; cough; sinusitis; ear, nose, and throat infections; and dizziness. Other side effects that have been reported, but were not as common, include rashes and allergic reactions, some of which were severe.

People with influenza (the flu), particularly children and adolescents, may be at an increased risk of seizures, confusion, or abnormal behavior early in their illness. These events may occur after beginning RELENZA or may occur when flu is not treated. These events are uncommon but may result in accidental injury to the patient. Therefore, patients should be observed for signs of unusual behavior and a healthcare professional should be contacted immediately if the patient shows any signs of unusual behavior.

This list of side effects is not complete. Your healthcare provider or pharmacist can discuss with you a more complete list of possible side effects with RELENZA. Talk to your healthcare provider promptly about any side effects you have.

Please refer to the section entitled "Important Safety Information About RELENZA" for additional information.

Should I get a flu shot?

RELENZA is not a substitute for a flu shot. You should receive an annual flu shot according to guidelines on immunization practices that your healthcare provider can share with you.

What if I am pregnant or nursing?

If you are pregnant or planning to become pregnant while taking RELENZA, talk to your healthcare provider before taking this medication. RELENZA is normally not recommended for use during pregnancy or nursing, as the effects on the unborn child or nursing infant are unknown.

How and where should I store RELENZA?

RELENZA should be stored at room temperature below 77°F (25°C). RELENZA is not in a childproof container. Keep RELENZA out of the reach of children. Discard the DISKHALER after finishing your treatment.

PATIENT INSTRUCTIONS FOR USE

IMPORTANT: Read Step-by-Step Instructions before using the DISKHALER®.

Be sure to take the dose your healthcare provider has prescribed.

BEFORE YOU START:

Please read the entire Patient Labeling for important information about the effects of RELENZA including the section “Important Safety Information About RELENZA” for information about the risk of breathing difficulties.

If RELENZA is prescribed for a child, dosing should be supervised by an adult who understands how to use RELENZA and has been instructed in its use by a healthcare provider.

Step-by-step instructions for using the DISKHALER®

Step A: Load the medicine into the DISKHALER

1. Start by pulling off the blue cover.
2. Always check inside the mouthpiece to make sure it is clear before each use. If foreign objects are in the mouthpiece, they could be inhaled and cause serious harm.
3. Pull the white mouthpiece by the edges to extend the white tray all the way.
4. Once the white tray is extended all the way, find the raised ridges on each side of it. Press in these ridges, both sides at the same time, and pull the whole white tray out of the DISKHALER body.
5. Place one silver medicine disk onto the dark brown wheel, flat side up. The four silver blisters on the underside of the medicine disk will drop neatly into the four holes in the wheel.
6. Push in the white tray as far as it will go. Now the DISKHALER is loaded with medicine.

Step B: Puncture the blister

Be sure to keep the DISKHALER level.

The DISKHALER punctures one blister of medicine at a time so you can inhale the right amount. It does not matter which blister you start with. Check to make sure that the silver foil is unbroken.

1. Be sure to keep the DISKHALER level so the medicine does not spill out.
2. Locate the half-circle flap with the name “RELENZA” on top of the DISKHALER.
3. Lift this flap from the outer edge until it cannot go any farther. Flap must be straight up for the plastic needle to puncture both the top and bottom of the silver medicine disk inside.
4. Keeping the DISKHALER level, click the flap down into place.

Step C: Inhale

1. Before putting the white mouthpiece into your mouth, breathe all the way out (exhale).
  Then put the white mouthpiece into your mouth. Be sure to keep the DISKHALER level so the medicine does not spill out.
2. Close your lips firmly around the mouthpiece. Be sure not to cover the small holes on either side of it.
3. Breathe in through your mouth steadily and as deeply as you can. Your breath pulls the medicine into your airways and lungs.
4. Hold your breath for a few seconds to help RELENZA stay in your lungs where it can work.

To take another inhalation, move to the next blister by following Step D below.

Once you’ve inhaled the number of blisters prescribed by your healthcare provider, replace the cover until your next dose.

Step D: Move the medicine disk to the next blister

1. Pull the mouthpiece to extend the white tray, without removing it.
2. Then push it back until it clicks. This pull-push motion rotates the medicine disk to the next blister.
3. To take your next inhalation, repeat Steps B and C.

If all four blisters in the medicine disk have been used, you are ready to start a new medicine disk (see Step A). Check to make sure that the silver foil is unbroken each time you are ready to puncture the next blister.

IMPORTANT INSTRUCTIONS

Read this entire leaflet before using RELENZA. Even if you have had a previous prescription for RELENZA, read this leaflet to see if any information has changed.

If you have the flu, the usual dose is 2 inhalations twice daily. To reduce the chance of getting the flu, the usual dose is 2 inhalations once daily. However, you must take the number of inhalations your healthcare provider has prescribed.

If you feel worse or develop new symptoms during or after treatment, or if your flu symptoms do not start to improve, stop using the medicine and contact your healthcare provider.

Keep out of reach of children.

Always check inside the mouthpiece to make sure it is clear before each use. If foreign objects are in the mouthpiece, they could be inhaled and cause serious harm.

Always replace the cover after each use.

Throw away the DISKHALER after treatment is completed.

This DISKHALER is for use only with RELENZA. Do not use the RELENZA DISKHALER device with FLOVENT® (fluticasone propionate) and do not use RELENZA with the FLOVENT DISKHALER device.

Store at 25°C (77°F); excursions permitted to 15° to 30°C (59° to 86°F) (see USP Controlled Room Temperature).

REMEMBER: This medicine has been prescribed for you by your healthcare provider. DO NOT give this medicine to anyone else.

RELENZA, FLOVENT, ROTADISK, and DISKHALER are registered trademarks of GlaxoSmithKline.

FLUMIST is a registered trademark of MedImmune, Inc.

PACKAGE LABEL

Principal Display Panel

NDC 68258-3030-1

RELENZA®

(ZANAMIVIR) INHALATION POWDER

5 ROTADISKS® each containing 4 blisters

5 mg

FOR ORAL INHALATION ONLY

Each blister contains 5 mg zanamivir with lactose.

Store at 25oC (77oF); excursions permitted to 15o to 30oC (59o to 86oF) (see USP Controlled Room Temperature).

Rx only

See prescribing information for dosage information.